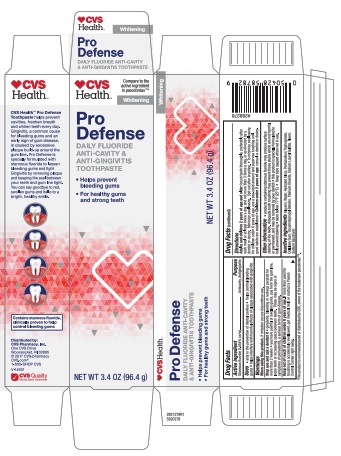 DRUG LABEL: CVS Pharmacy
NDC: 69842-872 | Form: PASTE, DENTIFRICE
Manufacturer: CVS Pharmacy
Category: otc | Type: HUMAN OTC DRUG LABEL
Date: 20250120

ACTIVE INGREDIENTS: STANNOUS FLUORIDE 0.454 g/100 g
INACTIVE INGREDIENTS: GLYCERIN; SACCHARIN SODIUM; WATER; SODIUM TRIPOLYPHOSPHATE ANHYDROUS; TITANIUM DIOXIDE; CARBOXYMETHYLCELLULOSE SODIUM; HYDRATED SILICA; COCAMIDOPROPYL BETAINE; SODIUM LAURYL SULFATE

5820278 CVS Pro Defense Whitening

Active ingredient

Stannous Fluoride (0.454% w/w)

Purpose

Anticavity/Antigingiviitis

Uses

- aids in the prevention of dental cavities
- helps control bleeding gums
- helps interfere with harmful effects of plaque associated with gingivitis

Warnings

When using this product, discontinue use if irritation occurs.

Stop use and ask a dentist if

- gingivitis, bleeding or redness persists for more than 2 weeks
- if you have painful or swollen gums, pus from the gum line, loose teeth or increasing space between teeth. These may be signs or symptoms of periodontis, a serious form of gum disease.

Keep out of reach of children under 6 years of age. If more than used for brushing is accidently swallowed, get medical help or contact a Poison Control Center right away.

Directions

Adults and children 2 years of age and older:

- Brush teeth thoroughly preferably after each meal or at least twice a day and not more than 3 times a day or as directed by a dentist or doctor. Minimize swallowing. Spit out after brushing.

- To minimize swallowing for children under 6 years of age, use a pea-sized amount and supervise brushing until good habits are established.

Children under 2 years of age: consult a dentist or doctor

Other information

- products containing Stannous Fluoride may cause surface staining of the teeth. Adequate tooth brushing may prevent these stains which are not harmful or permanent, and may be removed by your dentist.
- This product is specially formulated to help prevent staining.
- Store below 77F (25C)
- Keep tube capped when not in use.

INACTIVE INGREDIENT

Inactive ingredients glycerin, water, hydrated silica, pentasodium triphosphate, cellulose gum, cocamidopropyl betaine, titanium dioxide, sodium lauryl sulfate, flavor, sodium saccharin

Distributed by: CVS Pharmacy, Inc.

One CVS Drive, Woonsocket, RI 02895

©2017 CVS/pharmacy

CVS.com 1-800-SHOP CVS